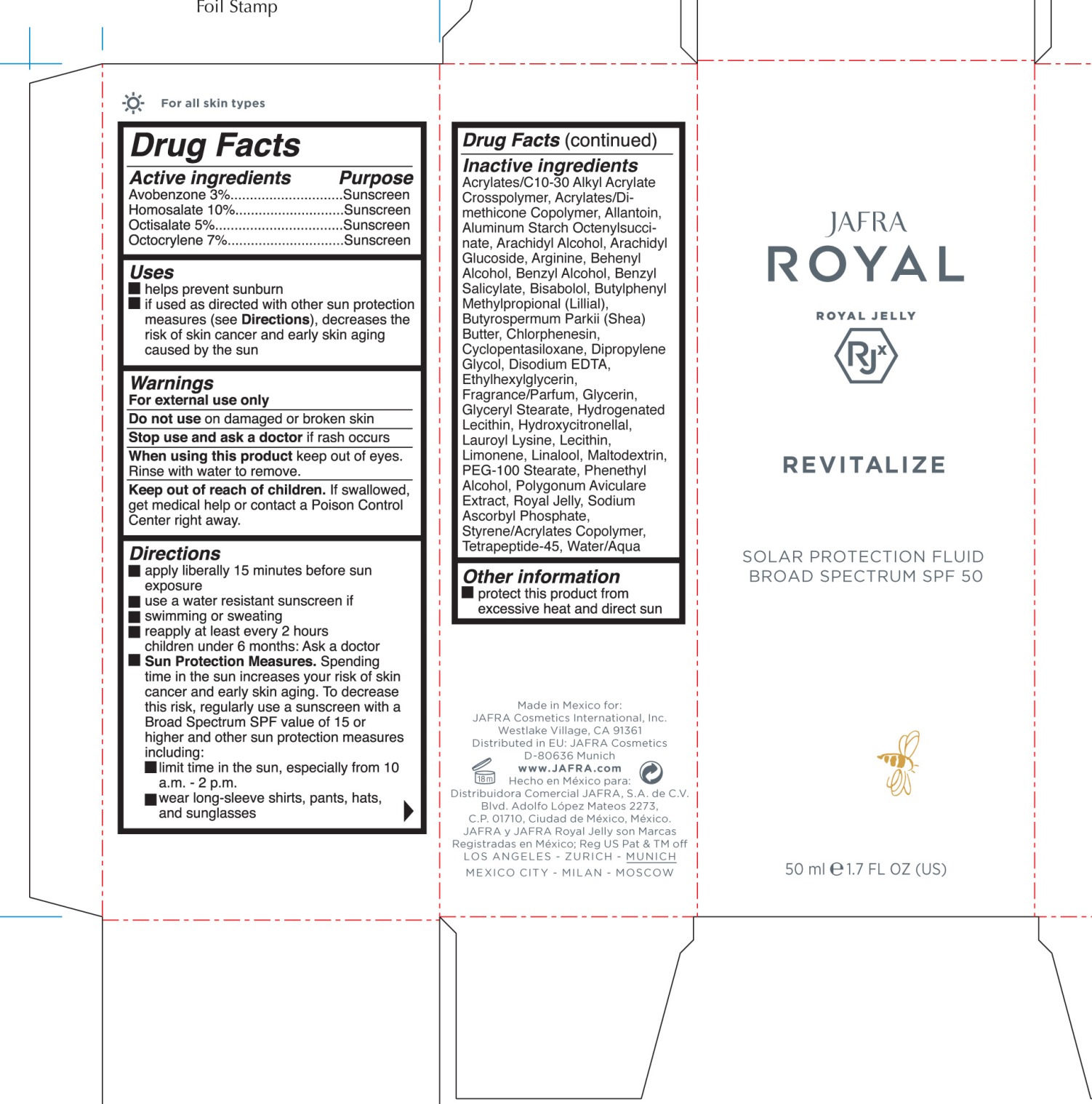 DRUG LABEL: Solar Protection Fluid
NDC: 68828-240 | Form: CREAM
Manufacturer: JAFRA COSMETICS INTERNATIONAL
Category: otc | Type: HUMAN OTC DRUG LABEL
Date: 20180205

ACTIVE INGREDIENTS: AVOBENZONE 3 g/100 mL; HOMOSALATE 10 g/100 mL; OCTISALATE 5 g/100 mL; OCTOCRYLENE 7 g/100 mL
INACTIVE INGREDIENTS: WATER; GLYCERYL MONOSTEARATE; PEG-100 STEARATE; ALUMINUM STARCH OCTENYLSUCCINATE; LAUROYL LYSINE; ARACHIDYL ALCOHOL; DOCOSANOL; ETHYLHEXYLGLYCERIN; ARACHIDYL GLUCOSIDE; BENZYL ALCOHOL; .ALPHA.-BISABOLOL, (+/-)-; ROYAL JELLY; CYCLOMETHICONE 5; COCOS NUCIFERA WHOLE; MORINGA OLEIFERA WHOLE; CARBOMER INTERPOLYMER TYPE A (ALLYL SUCROSE CROSSLINKED); EDETATE DISODIUM; ALLANTOIN; ARGININE; CHLORPHENESIN; CHICORY ROOT; KAPPAPHYCUS ALVAREZII; GLYCERIN; POLYGONUM AVICULARE TOP; SODIUM ASCORBYL PHOSPHATE; BENZYL SALICYLATE; LIMONENE, (+/-)-; HYDROXYCITRONELLAL; BUTYLPHENYL METHYLPROPIONAL; LINALOOL, (+/-)-

Royal Jelly - Solar Protection Fluid Broad Spectrum SPF 50

Active Ingredients Purpose

Avobenzone 3% Sunscreen

Homosalate 10% Suncreen

Octisalate 5% Suncreen

Octocrylene 7% Sunscreen

Uses

- Helps prevent sunburn
- if used as directed with other sun protection measures (see Directions), decreases the risk of skin cancer and early skin aging caused by the sun

Keep out of reach of children. If swallowed, get medical help or contact a Poison Control Center right away

Stop use and ask a doctor if rash occurs

Warnings

- For external use only
- Do not use on damaged or broken skin
- when using this product keep out of eyes. Rinse with water to remove.

Directions

- apply liberally 15 minutes before sun exposure
- use a water resistant sunscreen if
- swimming or sweating
- reapply at least every 2 hours children under 6 months: Ask a doctor
- Sun Protection Measures. Spending time in the sun icreases your risk of skin cancer and early skin aging. To decrease this risk, regularly use a sunscreen with a Broad Specturm SPF 15 or higher and other sun protection measures including:
- limit time in the sun, especially from 10 a.m. - 2 p.m.
- Wear long-sleeve shirts, pants, hats, and sunglasses

INACTIVE INGREDIENT

Water/Aqual, Styrene/Acrylate Copolymer, Glyceryl Stearate, PEG-100 Stearate, Aluminum Starch Octenylsuccinate, Lauroyl Lysine, Arachidyl Alcohol, Behenyl Alcohol, Arachidyl Glucoside, Ethylhexylglycerin, Benzyl Alcohol, Bisabolol, Royal Jelly, Cyclopentasiloxane, Acrylates/Dimethicon Copolymer, Cocos Nucifera, Moringa Oleifera, Fragrance/Parfum, Acrylates/C10-30 Alkyl Acrylate Crosspolymer, Disodium EDTA, Allantoin, Arginine, Chlorphenesin, Cichorium Intybus (Chicory) Root Extract, Kappaphycus Alvarezii Extract, Glycerin, Polygonum Aviculare Extract, Sodium Ascorbyl Phosphate, Benzyl Salicylate, Limonene, Hydroxycitronellal, Butylphenyl Methylpropional (Lillial), Linalool

PACKAGE LABEL

JAFRA

Royal Jelly

Solar Protection Fluid

Broad Spectrum SPF 50

50 ml 1.7 FL OZ (US)